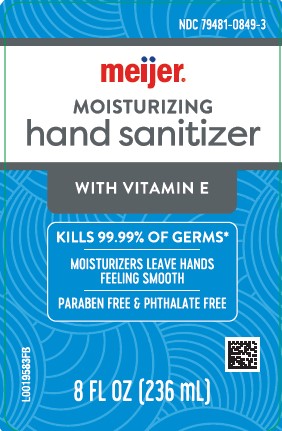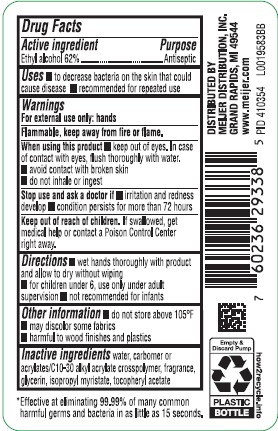 DRUG LABEL: Alcohol
NDC: 79481-0849 | Form: LIQUID
Manufacturer: Meijer, Inc.
Category: otc | Type: HUMAN OTC DRUG LABEL
Date: 20260219

ACTIVE INGREDIENTS: ALCOHOL 62 mL/100 mL
INACTIVE INGREDIENTS: WATER; CARBOMER HOMOPOLYMER, UNSPECIFIED TYPE; CARBOMER INTERPOLYMER TYPE A (ALLYL SUCROSE CROSSLINKED); GLYCERIN; ISOPROPYL MYRISTATE; TOCOPHEROL

Meijer 849.001/849AB-BA
Moisturizing Hand Sanitizer

Active ingredient

Ethyl Alcohol 62%

Purpose

Antiseptic

Uses

- to decrease bacteria on the skin that could cause disease
- recommended for repeated use

Warnings

For exterenal use only: hands

Flammable, keep away from fire or flame.

When using this product

- keep out of eyes. In case of contact with eyes, flush thoroughly with water.
- avoid contact with broken skin
- do not inhale or ingest

Stop use and ask a doctor if

- irritation and redness develop
- condition persists for more than 72 hours

Keep out of reach of children.

If swallowed, get medical help or contact a Poison Control Center right away.

Directions

- wet hands thoroughly with product and allow to dry without wiping
- for children under 6, use only under adult supervision
- not recommended for infants

Other information

- do not store above 105⁰F
- may discolor some fabrics
- harmful to wood finishes and plastics

Inactive ingredients

water, carbomer or acrylates/C10-30 alkyl acrylate crosspolymer, fragrance, glycerin, isopropyl myristate, tocopheryl acetate

Claims

*Effective at eliminating 99.99% of many common harmful germs and bacteria in as little as 15 seconds.

Adverse Reaction

DISTRIBUTED BY

MEIJER DISTRIBUTION, INC.

GRAND RAPIDS, MI 49544

www.meijer.com

Empty & Discard Pump

PLASTIC BOTTLE

how2recycle.info

Principal display panel

NDC 79481-0849-3

meijer®

MOISTURIZING

hand sanitizer

WITH VITAMIN E

KILLS 99.99% OF GERMS*

MOISTURIZERS LEAVE HANDS FEELINGS SMOOTH

PARABEN FREE & PHTHALATE FREE

8 FL OZ (236 mL)